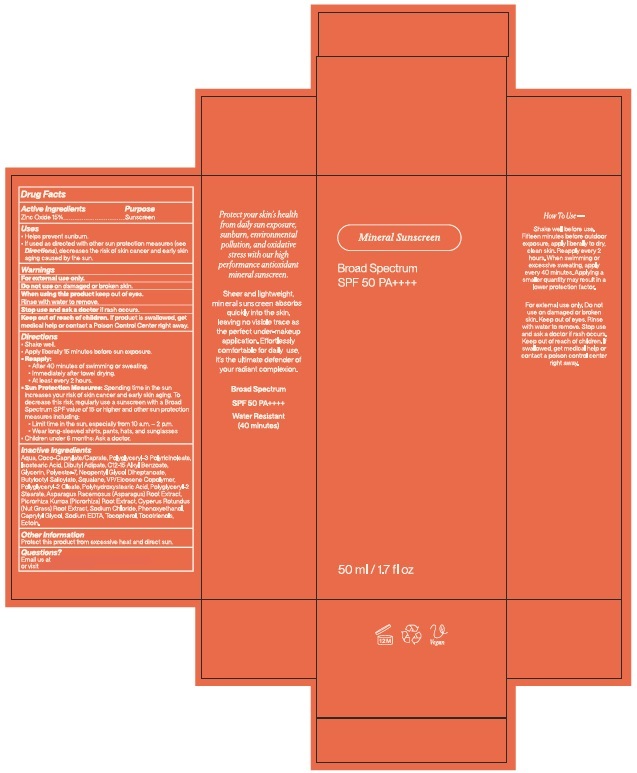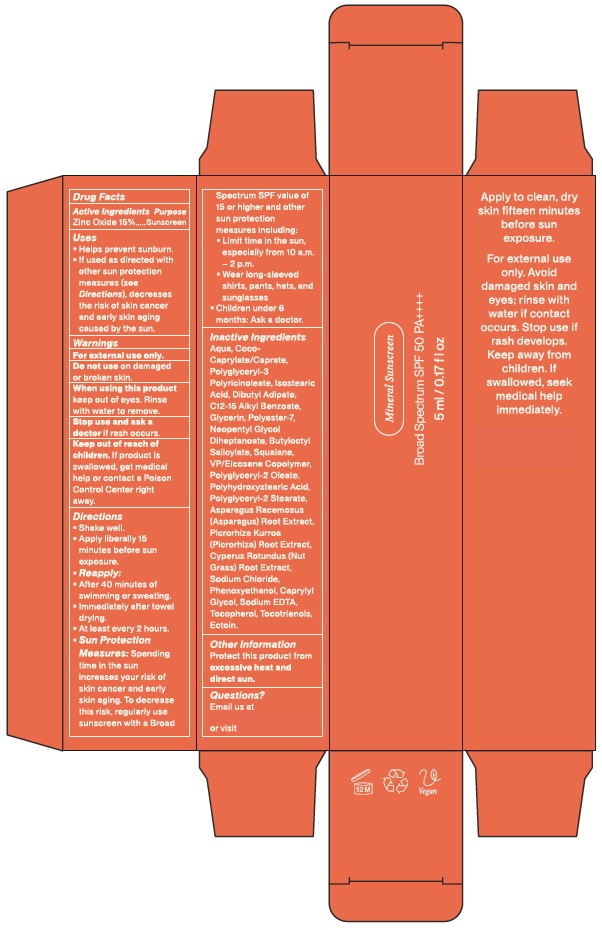 DRUG LABEL: Mineral Sunscreen
NDC: 73492-152 | Form: LOTION
Manufacturer: ALAINA HEALTHCARE PRIVATE LIMITED
Category: otc | Type: HUMAN OTC DRUG LABEL
Date: 20251212

ACTIVE INGREDIENTS: ZINC OXIDE 15 g/100 mL
INACTIVE INGREDIENTS: AQUA; COCO-CAPRYLATE/CAPRATE; POLYGLYCERYL-3 PENTARICINOLEATE; ISOSTEARIC ACID; DIBUTYL ADIPATE; C12-15 ALKYL BENZOATE; GLYCERIN; POLYESTER-7; NEOPENTYL GLYCOL DIHEPTANOATE; BUTYLOCTYL SALICYLATE; SQUALANE; VINYLPYRROLIDONE/EICOSENE COPOLYMER; POLYGLYCERYL-2 OLEATE; POLYHYDROXYSTEARIC ACID (2300 MW); POLYGLYCERYL-2 STEARATE; ASPARAGUS RACEMOSUS ROOT; PICRORHIZA KURROA ROOT; CYPERUS ROTUNDUS ROOT; SODIUM CHLORIDE; PHENOXYETHANOL; CAPRYLYL GLYCOL; EDETATE SODIUM; TOCOTRIENOLS; ECTOIN; TOCOPHEROL

Mineral Sunscreen
Broad Spectrum SPF 50 PA++++

Active ingredients

Zinc Oxide 15%

Purpose

Sunscreen

Uses

- Helps prevent sunburn.
- If used as directed with other sun protection measures (see Directions), decreases the risk of skin cancer and early skin aging caused by the sun.

Warnings

For external use only.

Do not useon damaged or broken skin.

When using this productkeep out of eyes.

Rinse with water to remove.

Stop use and ask a doctorif rash occurs.

Keep out of reach of children.If product is swallowed, get medical help or contact a Poison Control Center right away.

Directions

- Shake well.
- Apply liberally 15 minutes before sun exposure.
- Reapply:
  - After 40 minutes of swimming or sweating.
  - Immediately after towel drying.
  - At least every 2 hours.

- Sun Protection Measures:Spending time in the sun increases your risk of skin cancer and early skin aging. To decrease this risk, regularly use a sunscreen with a broad spectrum SPF value of 15 or higher and other sun protection measures including:
  - Limit time in the sun, especially from 10 a.m. - 2 p.m.
  - Wear long-sleeved shirts, pants, hats and sunglasses.
  - Children under 6 months: ask a doctor.

Inactive Ingredients

Aqua, Coco-Caprylate/Caprate, Polyglyceryl-3 Polyricinoleate, Isostearic Acid, Dibutyl Adipate, C12-15 Alkyl Benzoate, Glycerin, Polyester-7, Neopentyl Glycol Diheptanoate, Butyloctyl Salicylate, Squalane, VP/Eicosene Copolymer, Polyglyceryl-2 Oleate, Polyhydroxystearic Acid, Polyglyceryl-2 Stearate, Asparagus Racemosus (Asparagus) Root Extract, Picrorhiza Kurroa (Picrorhiza) Root Extract, Cyperus Rotundas (Nut Grass) Root Extract, Sodium Chloride, Phenoxyethanol, Caprylyl Glycol, Sodium EDTA, Tocopherol, Tocotrienols, Ectoin.

Other Information

Protect this product from excessive heat and direct sun.

Questions?

Email us at or visit

PACKAGE LABEL

Mineral Sunscreen Broad Spectrum SPF 50 PA++++ 5 mL/0.17 fl.OZ

Mineral Sunscreen Broad Spectrum SPF 50 PA++++ 50 mL/1.7 fl.OZ